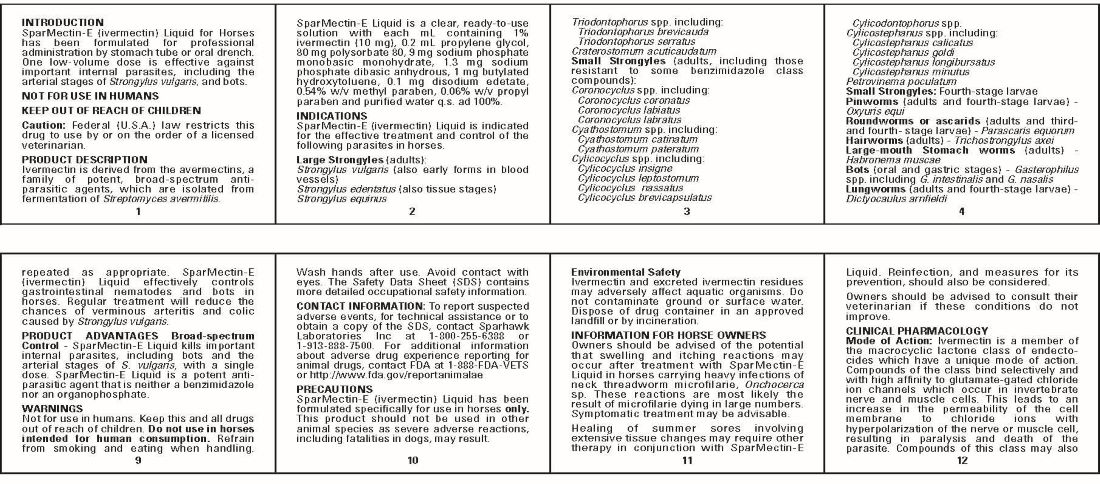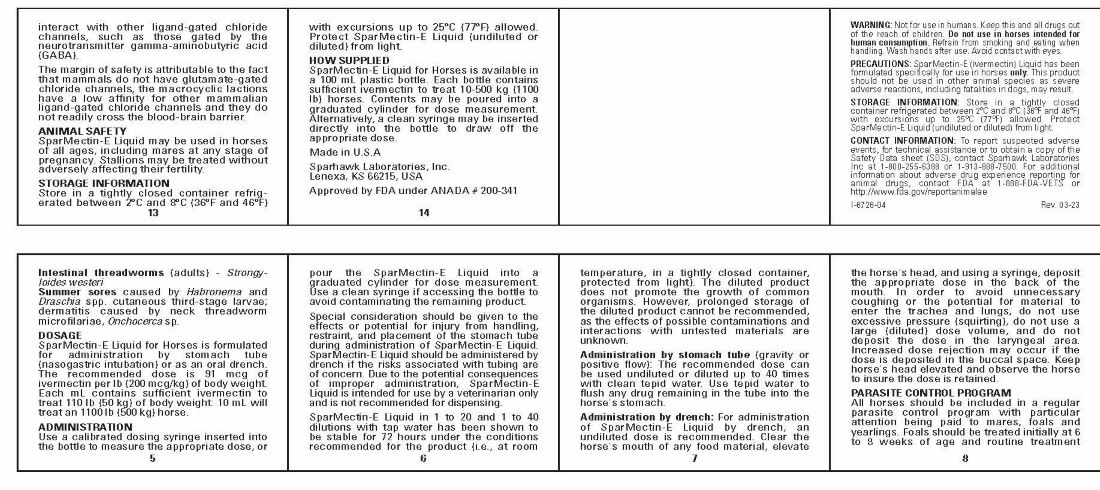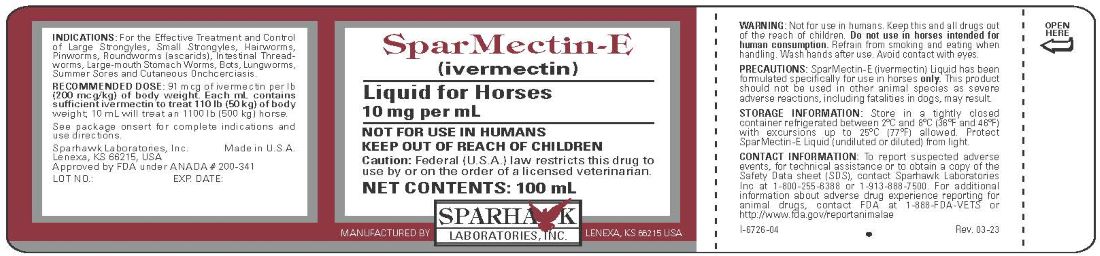 DRUG LABEL: SPARMECTIN
NDC: 58005-725 | Form: LIQUID
Manufacturer: Sparhawk Laboratories, Inc.
Category: animal | Type: PRESCRIPTION ANIMAL DRUG LABEL
Date: 20230721

ACTIVE INGREDIENTS: IVERMECTIN 10 mg/1 mL

SparMectin-E

DESCRIPTION

(ivermectin)

Liquid for Horses
10 mg per mL

NOT FOR USE IN HUMANS
KEEP OUT OF REACH OF CHILDREN

Caution: Federal (U.S.A.) law restricts this drug to use by or on the order of a licensed veterinarian.

INTRODUCTION

SparMectin-E (ivermectin) Liquid for Horses has been formulated for professional administration by stomach tube or oral drench. One low-volume dose is effective against important internal parasites, including the arterial stages of Strongylus vulgaris, and bots.

PRODUCT DESCRIPTION

Ivermectin is derived from the avermectins, a family of potent, broad-spectrum anti-parasitic agents, which are isolated from fermentation of Streptomyces avermitilis.

SparMectin-E Liquid is a clear, ready-to-use solution with each mL containing 1% ivermectin (10 mg), 0.2 mL propylene glycol, 80 mg polysorbate 80, 9 mg sodium phosphate monobasic monohydrate, 1.3 mg sodium phosphate dibasic anhydrous, 1 mg butylated hydroxytoluene, 0.1 mg disodium edetate, 0.54% w/v methyl paraben, 0.06% w/v propyl paraben and purified water q.s. ad 100%.

INDICATIONS

SparMectin-E (ivermectin) Liquid is indicated for the effective treatment and control of the following parasites in horses.

Large Strongyles (adults):
Strongylus vulgaris (also early forms in blood vessels)
Strongylus edentatus (also tissue stages)
Strongylus equinus
Triodontophorus spp. including:
Triodontophorus brevicauda
Triodontophorus serratus
Craterostomum acuticaudatum
Small Strongyles (adults, including those resistant to some benzimidazole class compounds):
Coronocyclus spp. including:
Coronocyclus coronatus
Coronocyclus labiatus
Coronocyclus labratus
Cyathostomum spp. including:
Cyathostomum catinatum
Cyathostomum pateratum
Cylicocyclus spp. including:
Cylicocyclus insigne
Cylicocyclus leptostomum
Cylicocyclus nassatus
Cylicocyclus brevicapsulatus
Cylicodontophorus spp.
Cylicostephanus spp. including:
Cylicostephanus calicatus
Cylicostephanus goldi
Cylicostephanus longibursatus
Cylicostephanus minutus
Petrovinema poculatum
Small Strongyles: Fourth-stage larvae
Pinworms (adults and fourth-stage larvae) - Oxyuris equi
Roundworms or ascarids (adults and third- and fourth-stage larvae) - Parascaris equorum
Hairworms (adults) - Trichostrongylus axei
Large-mouth Stomach worms (adults) - Habronema muscae
Bots (oral and gastric stages) - Gasterophilus spp. including G. intestinalis and G. nasalis
Lungworms (adults and fourth-stage larvae) - Dictyocaulus arnfieldi
Intestinal threadworms (adults) - Strongyloides westeri
Summer sores caused by Habronema and Draschia spp. cutaneous third-stage larvae; dermatitis caused by neck threadworm microfilariae, Onchocerca sp.

DOSAGE

SparMectin-E Liquid for Horses is formulated for administration by stomach tube (nasogastric intubation) or as an oral drench. The recommended dose is 91 mcg of ivermectin per lb (200 mcg/kg) of body weight. Each mL contains sufficient ivermectin to treat 110 lb (50 kg) of body weight: 10 mL will treat an 1100 lb (500 Kg) horse.

ADMINISTRATION

Use a calibrated dosing syringe inserted into the bottle of measure the appropriate dose, or pour the SparMectin-E Liquid into a graduated cylinder for dose measurement. Use a clean syringe if accessing the bottle to avoid contaminating the remaining product.

Special consideration should be given to effects of potential for injury from handling, restraint, and placement of the stomach tube during administration of SparMectin-E Liquid. SparMectin-E Liquid should be administered by drench if the risks associated with tubing are of concern. Due to the potential consequences of improper administration, SparMectin-E Liquid is intended for use by a veterinarian only and is not recommended for dispensing.

SparMectin-E Liquid in 1 to 20 and 1 to 40 dilutions with tap water has been shown to be stable for 72 hours under the conditions recommended for the product (i.e., at room temperature, in a tightly closed container, protected from light). The diluted product does not promote the growth of common organisms. However, prolonged storage of the diluted product cannot be recommended, as the effects of possible contaminations and interactions with untested materials are unknown.

Administration by stomach tube (gravity or positive flow): The recommended dose can be used undiluted or diluted up to 40 times with clean tepid water. Use tepid water to flush any drug remaining in the tube into the horse's stomach.

Administration by drench: For administration of SparMectin-E by drench, an undiluted dose is recommended. Clear the horse's mouth of any food material, elevate the horse's head, and using a syringe, deposit the appropriated dose in the back of the mouth. In order to avoid unnecessary coughing or the potential for material to enter the trachea and lungs, do not use excessive pressure (squirting), do not use a large (diluted) dose volume, and do not deposit the dose in the laryngeal area. Increased dose rejection may occur if the dose is deposited in the buccal space. Keep horse's head elevated and observe the horse to insure the dose is retained.

INSTRUCTIONS FOR USE

PARASITE CONTROL PROGRAM

All horses should be included in a regular parasite control program with particular attention being paid to mares, foals and yearlings. Foals should be treated initially at 6 to 8 weeks of age and routine treatment repeated as appropriate. SparMectin-E (ivermectin) Liquid effectively controls gastrointestinal nematodes and bots in horses. Regular treatment will reduce the chances of verminous arteritis and colic caused by Strongylus vulgaris.

PRODUCT ADVANTAGES Broad-spectrum Control

SparMectin-E Liquid kills important internal parasites, including bots and the arterial stages of S. vulgaris, with a single dose. SparMectin-E Liquid is a potent anti-parasitic agent that is neither a benzimidazole nor a organophosphate.

WARNINGS

Not for use in humans. Keep this and all drugs out of the reach of children. Do not use in horses intended for human consumption. Refrain from smoking and eating when handling. Wash hands after use. Avoid contact with eyes. The Safety Data Sheet (SDS) contains more detailed occupational safety information.

CONTACT INFORMATION

To report suspected adverse events, for technical assistance or to obtain a copy of the SDS, contact Sparhawk Laboratories Inc at 1-800-255-6388 or 1-913-888-7500. For additional information about adverse drug experience reporting for animal drugs, contact FDA at 1-888-FDA-VETS or http://www.fda.gov/reportanimalae

PRECAUTIONS

SparMectin-E (ivermectin) Liquid has been formulated specifically for use in horses only. This product should not be used in other animal species as severe adverse reactions, including fatalities in dogs, may result.

ENVIRONMENTAL SAFETY

Ivermectin and excreted ivermectin residues may adversely affect aquatic organisms. Do not contaminate ground or surface water. Dispose of drug container in an approved landfill or by incineration.

INFORMATION FOR HORSE OWNERS

Owners should be advised of the potential that swelling and itching reactions may occur after treatment with SparMectin-E Liquid in horses carrying heavy infections of neck threadworm microfilarie, Onchocerca sp. These reactions are most likely the result of microfilarie dying in large numbers. Symptomatic treatment may be advisable.

Healing of summer sores involving extensive tissue changes may require other therapy in conjunction with SparMectin-E Liquid. Reinfection, and measures for its prevention, should also be considered.

Owners should be advised to consult their veterinarian if these conditions do no improve.

CLINICAL PHARMACOLOGY

Mode of Action: Ivermectin is a member of the macrocyclic lactone class of endectocides which have a unique mode of action. Compounds of the class bind selectively and with high affinity to glutamate-gated chloride ion channels which occur in invertebrate nerve and muscle cells. This leads to an increase in the permeability of the cell membrane to chloride ions with hyperpolarization of the never or muscle cell, resulting in paralysis and death of the parasite. Compounds of this class may also interact with other ligand-gated chloride channels, such as those gated by the neurotransmitter gamma-aminobutyric acid (GABA).

The margin of safety is attributable to the fact that mammals do not have glutamate-gated chloride channels, the macrocyclic lactions have a low affinity for other mammalian ligand-gated chloride channels and they do not readily cross the blood-brain barrier.

ANIMAL SAFETY

SparMectin-E Liquid may be used in horses of all ages, including mares at any stage of pregnancy. Stallions may be treated without adversely affecting their fertility.

STORAGE INFORMATION

Store in a tightly closed container refrigerated between 2oC and 8oC (36oF and 46oF) with excursions up to 25oC (77oF) allowed. Protect SparMectin-E Liquid (undiluted or diluted) from light.

HOW SUPPLIED

SparMectin-E Liquid for Horses is available in a 100 mL plastic bottle. Each bottle contains sufficient ivermectin to treat 10-500 kg (1100 lb) horses. Contents may be poured into a graduated cylinder for dose measurements. Alternatively, a clean syringe may be inserted directly into the bottle to draw off the appropriate dose.